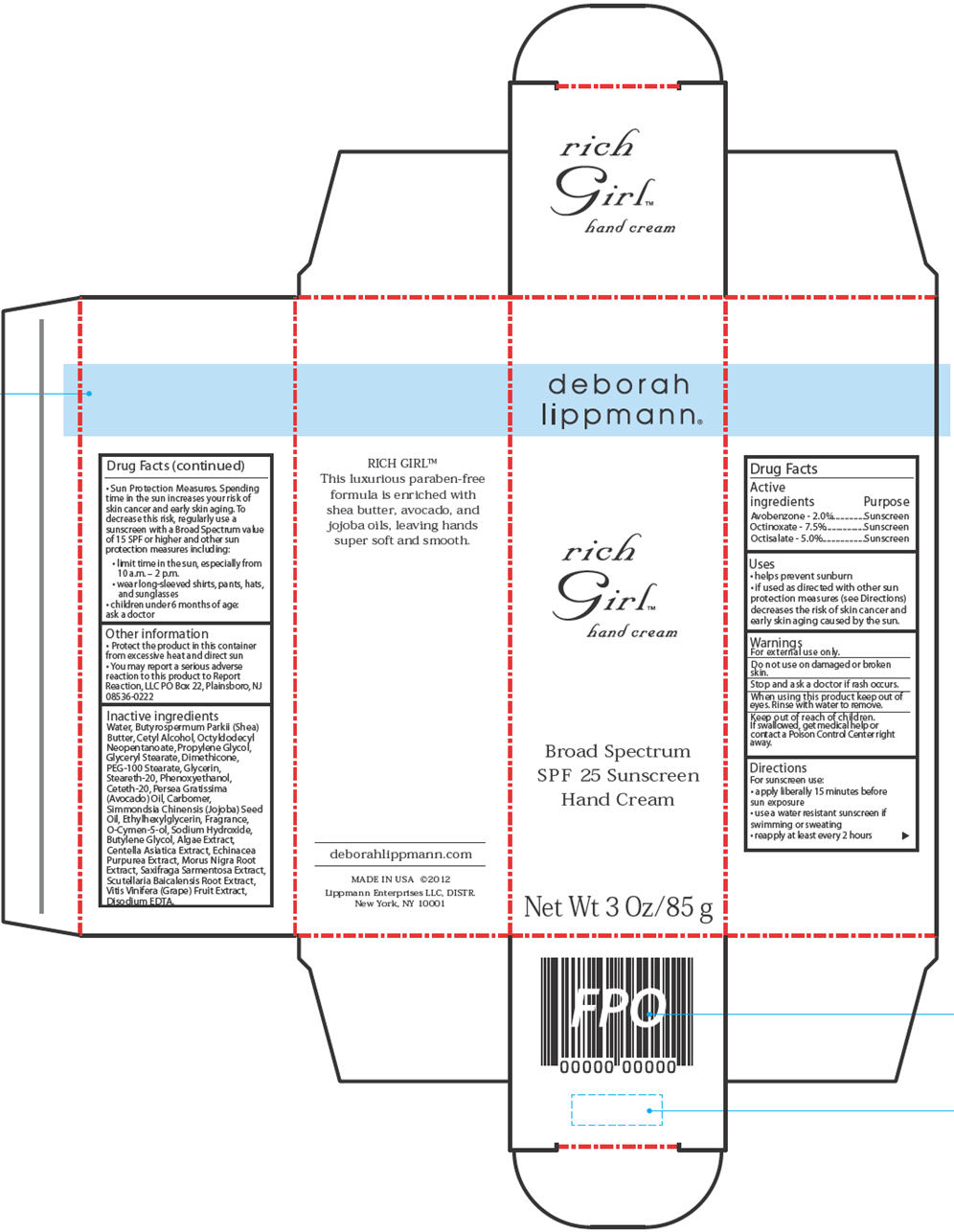 DRUG LABEL: Rich Girl
NDC: 49991-001 | Form: CREAM
Manufacturer: SPECIALITY COSMETICS POLI
Category: otc | Type: HUMAN OTC DRUG LABEL
Date: 20241007

ACTIVE INGREDIENTS: AVOBENZONE 2 g/100 g; OCTINOXATE 7.5 g/100 g; OCTISALATE 5 g/100 g
INACTIVE INGREDIENTS: CETYL ALCOHOL; OCTYLDODECYL NEOPENTANOATE; PROPYLENE GLYCOL; GLYCERYL MONOSTEARATE; DIMETHICONE; PEG-100 STEARATE; GLYCERIN; STEARETH-20; PHENOXYETHANOL; CETETH-20; AVOCADO OIL; JOJOBA OIL; ETHYLHEXYLGLYCERIN; O-CYMEN-5-OL; SODIUM HYDROXIDE; BUTYLENE GLYCOL; CENTELLA ASIATICA; ECHINACEA PURPUREA; MORUS NIGRA ROOT; SAXIFRAGA STOLONIFERA LEAF; SCUTELLARIA BAICALENSIS ROOT; WINE GRAPE; EDETATE DISODIUM; WATER; SHEA BUTTER

Rich Girl™ Hand Cream

Drug Facts

ACTIVE INGREDIENT

Active ingredients | Purpose
Avobenzone - 2.0% | Sunscreen
Octinoxate - 7.5% | Sunscreen
Octisalate - 5.0% | Sunscreen

Uses

- helps prevent sunburn
- if used as directed with other sun protection measures (see Directions) decreases the risk of skin cancer and early skin aging caused by the sun.

Warnings

For external use only.

Do not use on damaged or broken skin.

Stop and ask a doctor if rash occurs.

When using this product keep out of eyes. Rinse with water to remove.

Keep out of reach of children. If swallowed, get medical help or contact a Poison Control Center right away.

Directions

For sunscreen use:

- apply liberally 15 minutes before sun exposure
- use a water resistant sunscreen if swimming or sweating
- reapply at least every 2 hours
- Sun Protection Measures. Spending time in the sun increases your risk of skin cancer and early skin aging. To decrease this risk, regularly use a sunscreen with a Broad Spectrum value of 15 SPF or higher and other sun protection measures including:
  - limit time in the sun, especially from 10 a.m. – 2 p.m.
  - wear long-sleeved shirts, pants, hats, and sunglasses
- children under 6 months of age: ask a doctor

Other information

- Protect the product in this container from excessive heat and direct sun
- You may report a serious adverse reaction to this product to Report Reaction, LLC PO Box 22, Plainsboro, NJ 08536-0222

Inactive ingredients

Water, Butyrospermum Parkii (Shea) Butter, Cetyl Alcohol, Octyldodecyl Neopentanoate, Propylene Glycol, Glyceryl Stearate, Dimethicone, PEG-100 Stearate, Glycerin, Steareth-20, Phenoxyethanol, Ceteth-20, Persea Gratissima (Avocado) Oil, Carbomer, Simmondsia Chinensis (Jojoba) Seed Oil, Ethylhexylglycerin, Fragrance, O-Cymen-5-ol, Sodium Hydroxide, Butylene Glycol, Algae Extract, Centella Asiatica Extract, Echinacea Purpurea Extract, Morus Nigra Root Extract, Saxifraga Sarmentosa Extract, Scutellaria Baicalensis Root Extract, Vitis Vinifera (Grape) Fruit Extract, Disodium EDTA.

Lippmann Enterprises LLC, DISTR.
New York, NY 10001

PRINCIPAL DISPLAY PANEL - 85 g Tube Carton

deborah
lippmann®

rich
Girl ™
hand cream

Broad Spectrum
SPF 25 Sunscreen
Hand Cream

Net Wt 3 Oz/85 g